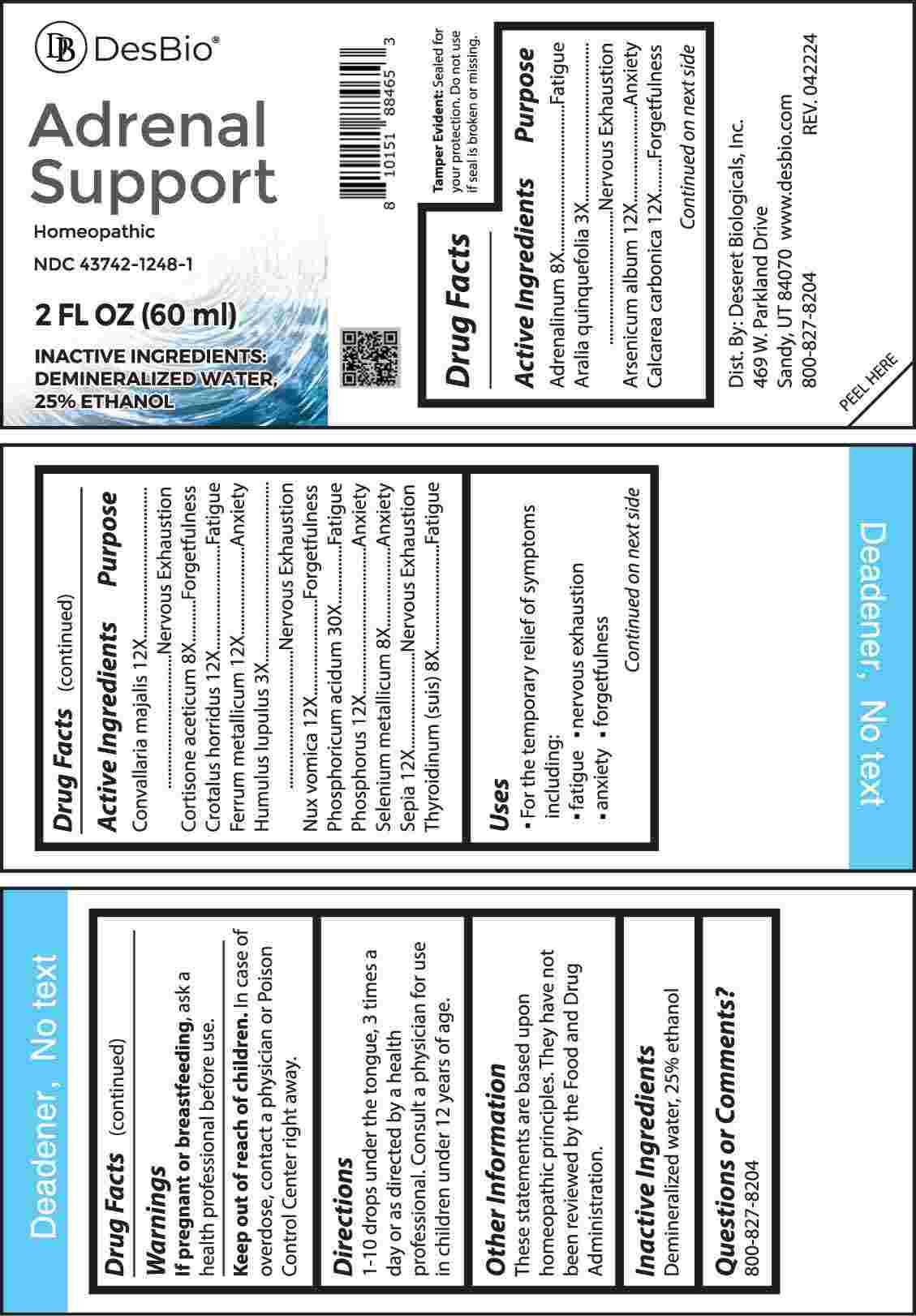 DRUG LABEL: Adrenal Support
NDC: 43742-1248 | Form: LIQUID
Manufacturer: Deseret Biologicals, Inc.
Category: homeopathic | Type: HUMAN OTC DRUG LABEL
Date: 20240729

ACTIVE INGREDIENTS: AMERICAN GINSENG 3 [hp_X]/1 mL; HOPS 3 [hp_X]/1 mL; EPINEPHRINE 8 [hp_X]/1 mL; CORTISONE ACETATE 8 [hp_X]/1 mL; SELENIUM 8 [hp_X]/1 mL; THYROID 8 [hp_X]/1 mL; ARSENIC TRIOXIDE 12 [hp_X]/1 mL; OYSTER SHELL CALCIUM CARBONATE, CRUDE 12 [hp_X]/1 mL; CONVALLARIA MAJALIS 12 [hp_X]/1 mL; CROTALUS HORRIDUS HORRIDUS VENOM 12 [hp_X]/1 mL; IRON 12 [hp_X]/1 mL; STRYCHNOS NUX-VOMICA SEED 12 [hp_X]/1 mL; PHOSPHORUS 12 [hp_X]/1 mL; SEPIA OFFICINALIS JUICE 12 [hp_X]/1 mL; PHOSPHORIC ACID 30 [hp_X]/1 mL
INACTIVE INGREDIENTS: WATER; ALCOHOL

DRUG FACTS:

ACTIVE INGREDIENTS:

Adrenalinum 8X, Aralia Quinquefolia 3X, Arsenicum Album 12X, Calcarea Carbonica 12X, Convallaria Majalis 12X, Cortisone Aceticum 8X, Crotalus Horridus 12X, Ferrum Metallicum 12X, Humulus Lupulus 3X, Nux Vomica 12X, Phosphoricum Acidum 30X, Phosphorus 12X, Selenium Metallicum 8X, Sepia 12X, Thyroidinum (Suis) 8X.

PURPOSE:

Adrenalinum - Fatigue, Aralia Quinquefolia – Nervous Exhaustion, Arsenicum Album - Anxiety, Calcarea Carbonica - Forgetfulness, Convallaria Majalis – Nervous Exhaustion, Cortisone Aceticum - Forgetfulness, Crotalus Horridus - Fatigue, Ferrum Metallicum - Anxiety, Humulus Lupulus – Nervous Exhaustion, Nux Vomica - Forgetfulness, Phosphoricum Acidum - Fatigue, Phosphorus - Anxiety, Selenium Metallicum - Anxiety, Sepia – Nervous Exhaustion, Thyroidinum (Suis) - Fatigue

USES:

• For the temporary relief of symptoms including:

• fatigue • nervous exhaustion • anxiety • forgetfulness

These statements are based upon homeopathic principles. They have not been reviewed by the Food and Drug Administration.

WARNINGS:

If pregnant or breast-feeding, ask a health professional before use.

Keep out of reach of children. In case of overdose, contact a physician or Poison Control Center right away.

Tamper Evident: Sealed for your protection. Do not use if seal is broken or missing.

KEEP OUT OF REACH OF CHILDREN:

In case of overdose, contact a physician or Poison Control Center right away.

DIRECTIONS:

1-10 drops under the tongue, 3 times a day or as directed by a health professional. Consult a physician for use in children under 12 years of age.

INACTIVE INGREDIENTS:

Demineralized water, 25% ethanol

QUESTIONS:

Dist. By: Deseret Biologicals, Inc.
469 W. Parkland Drive
Sandy, UT 84070

www.desbio.com

800-827-8204

PACKAGE LABEL DISPLAY:

Des Bio

Adrenal Support

Homeopathic

NDC 43742-1248-1

2 FL OZ (60 ml)